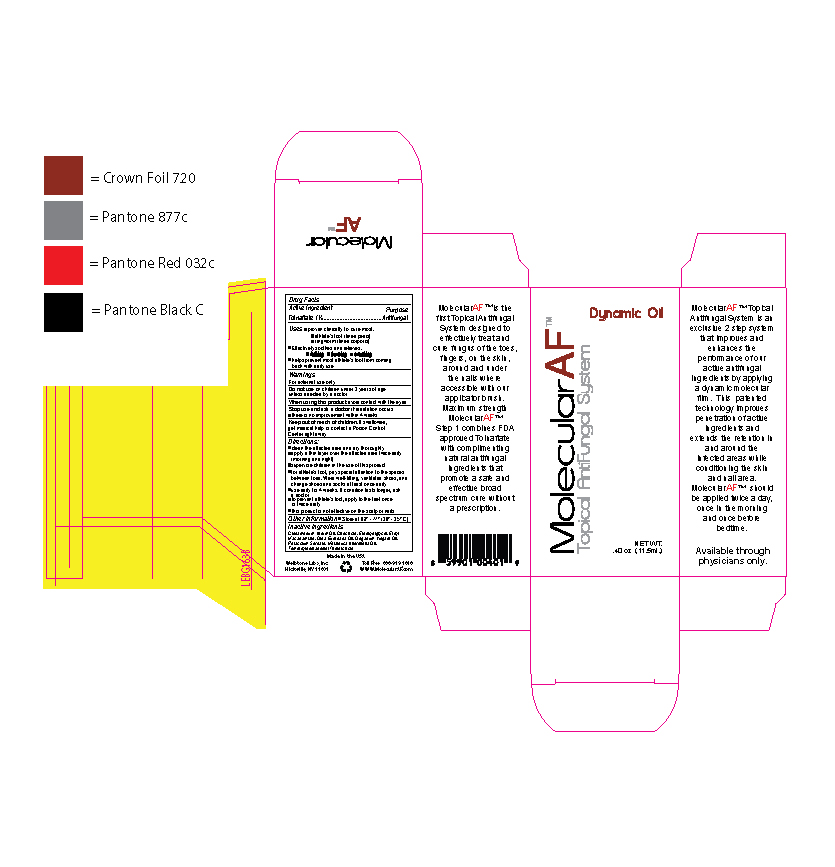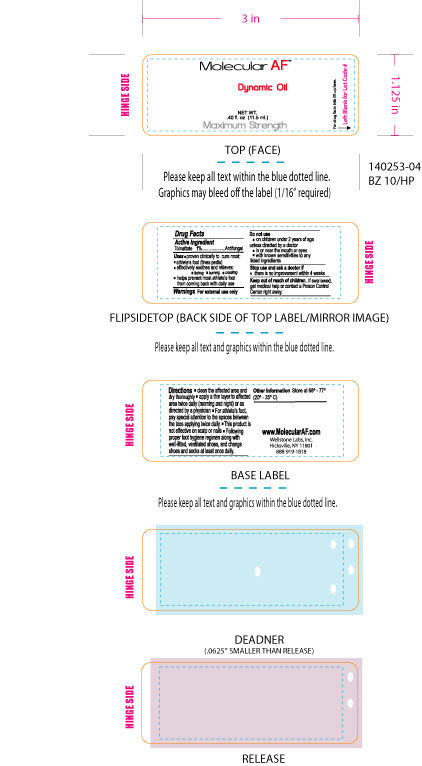 DRUG LABEL: Molecular AF
NDC: 76348-401 | Form: OIL
Manufacturer: Renu Laboratories, LLC
Category: otc | Type: HUMAN OTC DRUG LABEL
Date: 20250203

ACTIVE INGREDIENTS: TOLNAFTATE 0.01 mg/1 mL
INACTIVE INGREDIENTS: CINNAMON OIL; CITRIC ACID MONOHYDRATE; POTASSIUM SORBATE; ETHYL MACADAMIATE; DIETHYLENE GLYCOL MONOETHYL ETHER; TEA TREE OIL; OLIVE OIL

MOLECULAR AF

Active Ingredient

Tolnaftate 1%

Purpose

Antifungal

Stop use and ask a doctor if

- there is no improvement within 4 weeks

Do not use

- on children under 2 years of age unless directed by a doctor

Keep out of reach of children. If swallowed, get medical help or contact a Poison Control Center right away.

QUESTIONS

www.MolecularAF.com

888-919-1818

Stop use and ask a doctor if

- irritation occurs
- there is no improvement within 4 weeks

STATEMENT OF IDENTITY

Molecular AF

Topical Antifungal System

Dynamic Oil

Other information Store at 68º - 77º

(20º - 25º C)

Directions:

- clean the affected area and dry thoroughly
- apply a thin layer over the affected area twice daily (morning and night)
- supervise children in the use of the product
- for athlete's foot, pay special attention to the spaces between toes. Wear well-fitting, ventilated shoes, and change shoes and socks at least once daily
- use daily for 4 weeks, if condition lasts longer, ask a doctor
- to prevent athlete's foot, apply to the feet once or twice daily
- this product is not effective on the scalp or nails

Warnings

For external use only

Do not use on children under 2 years of age unless directed by a doctor

When using this product avoid contact with the eyes

INACTIVE INGREDIENT

CITRIC ACID MONOHYDRATE, DIETHYLENE GLYCOL MONOETHYL ETHER, ETHYL MACADAMIATE

OLIVE OIL, POTASSIUM SORBATE, TEA TREE OIL

INDICATIONS AND USAGE

Uses proven clinically to cure most:

athlete's foot (tinea pedis)

ringworm (tinea corporis)

effectively soothes and relieves:

itching

burning

cracking

helps prevent most athlete's foot from coming back with daily use

PACKAGE LABEL

This artwork is the peel-back label for Molecular AF.

THE ARTWORK BELOW IS THE BOX PACKAGE FOR MOLECULAR OIL